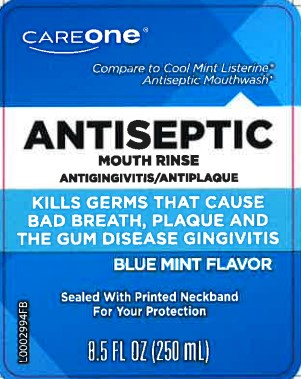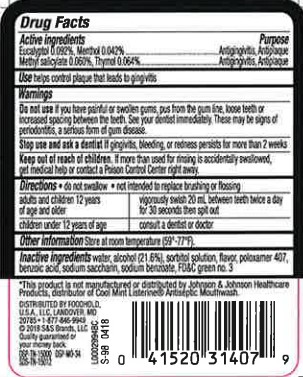 DRUG LABEL: Antispetic
NDC: 72476-664 | Form: MOUTHWASH
Manufacturer: Retail Business Services, LLC
Category: otc | Type: HUMAN OTC DRUG LABEL
Date: 20260206

ACTIVE INGREDIENTS: EUCALYPTOL 0.92 mg/1 mL; MENTHOL 0.42 mg/1 mL; METHYL SALICYLATE 0.6 mg/1 mL; THYMOL 0.64 mg/1 mL
INACTIVE INGREDIENTS: ALCOHOL; SORBITOL; POLOXAMER 407; BENZOIC ACID; SACCHARIN SODIUM; SODIUM BENZOATE; FD&C GREEN NO. 3; WATER

Care One 664.003 664AT rev 2 664AU
Blue Mint Mouthrinse

Active ingredients

Eucalyptol 0.092%

Menthol 0.042%

Methyl salicylate 0.060%

Thymol 0.064%

Purpose

Antigingivitis, Antiplaque

Use

helps control plaque that leads to gingivitis

Warnings

for this product

Do not use

if you have painful or swollen gums, pus from the gum line, loose teeth or increased spacing between the teeth. See your dentist immediately. These may be signs of periodontitis, a serious form of gum disease.

Stop use and ask a dentist if

gingivitis, bleeding, or redness persists for more than 2 weeks.

Keep out of reach of children.

If more than used for rinsing is accidentally swallowed, get medical help or contact a Poison Control Center right away.

Directions

- do not swallow
- not intended to replace brushing or flossing

adults and children 12 years of age and older - vigorously swish 20 mL (2/3 FL OZ or 4 teaspoonfuls) between teeth for 30 seconds then spit out

children under 12 years of age - consult a dentist or doctor

Other information

Store at room temperature (59° - 77°F)

Inactive ingredients

water, alcohol 21.6%, sorbitol solution, flavor, poloxamer 407, benzoic acid, sodium saccharin, sodium benzoate, FD&C green no.3

ADVERSE REACTION

*This product is not manufactured or distributed by Johnson & Johnson Healthcare Products, distributor of Cool Mint Listerine Antiseptic Mouthwash.

Distributed by Foodhold USA, LLC

Landover, MD 20785

1-877-845-9949

(c)2018 S&S Brands, LLC

Quality guaranteed or your money back

DSP-TN-15000 DSP-MO-34 SDS-TN-15012

Principal display panel

Care One

Compare to Cool Mint Listerine Antiseptic Mouthwash*

Antiseptic Mouth rinse

Antigingivitis/Antiplaque

Kills Germs that Cause bad breath, plaque and the gum disease gingivitis

Blue Mint flavor

Sealed with printed neckband for your protection

8.5 FL OZ (250 mL)